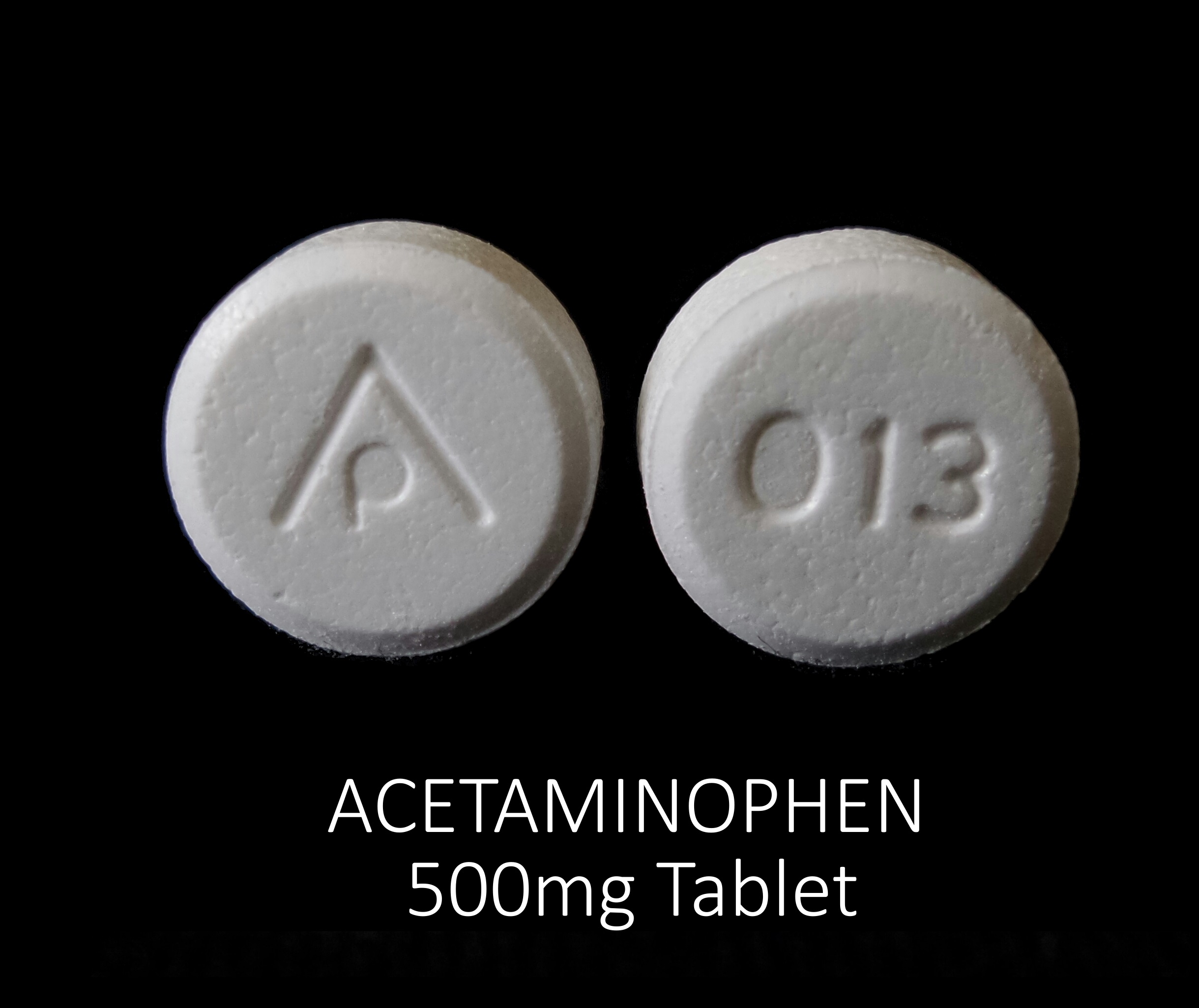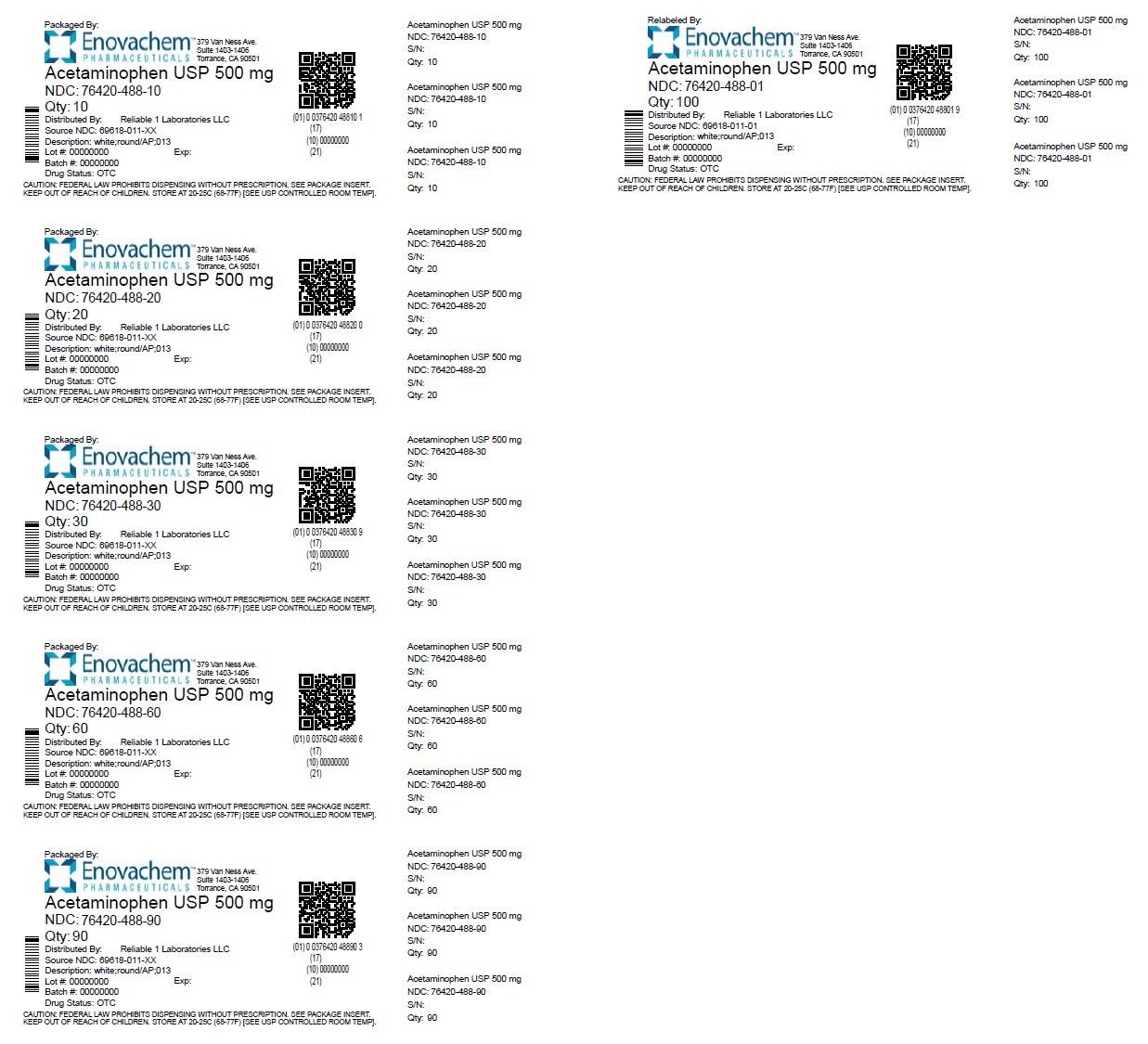 DRUG LABEL: ACETAMINOPHEN 500 MG
NDC: 76420-488 | Form: TABLET
Manufacturer: ASCLEMED USA INC.
Category: otc | Type: HUMAN OTC DRUG LABEL
Date: 20251014

ACTIVE INGREDIENTS: ACETAMINOPHEN 500 mg/1 1
INACTIVE INGREDIENTS: SODIUM STARCH GLYCOLATE TYPE A POTATO; POVIDONE; STARCH, PREGELATINIZED CORN; STEARIC ACID

ACETAMINOPHEN 500 MG TABLET

Drug Facts

Active ingredient (in each tablet)

Acetaminophen USP, 500 mg

Purpose

Pain reliever/fever reducer

Uses

- temporarily relieves minor aches and pains due to:
- headache
- muscular aches
- backache
- minor pain of arthritis
- the common cold
- toothache
- premenstrual and menstrual cramps

- temporarily reduces fever

Warnings

Liver warning:This product contains acetaminophen. Severe liver damage may occur if you take

- more than 4,000 mg of acetaminophen in 24 hours which is the maximum daily amount
- with other drugs containing acetaminophen
- 3 or more alcoholic drinks every day while using this product

Allergy alert:acetaminophen may cause severe skin reactions. Symptoms may include:

- skin reddening
- blisters
- rash

- If a skin reaction occurs, stop use and seek medical help right away.

DO NOT USE

Do not usewith any other drug containing acetaminophen (prescription or nonprescription). If you are not sure whether a drug contains acetaminophen, ask a doctor or pharmacist.

Ask a doctor before use if you haveliver disease

Ask a doctor or pharmacist before use if you aretaking the blood thinning drug warfarin

Stop use and ask a doctor if

- pain gets worse or lasts more than 10 days
- fever gets worse or lasts more than 3 days
- new symptoms occur
- redness or swelling is present

These could be signs of a serious condition.

PREGNANCY OR BREAST FEEDING

If pregnant or breast-feeding,ask a health professional before use.

Keep out of reach of children.

Overdose warning:Taking more than the recommended dose (overdose) may cause liver damage. In case of overdose, get medical help or contact a Poison Control Center right away. Quick medical attention is critical for adults as well as for children even if you do not notice any signs or symptoms.

Directions

do not take more than directed (see overdose warning)

adults & children 12 years and over:

- take 1 tablet every 3-4 hours or 2 tablets every 6 hours while symptoms last
- do not take more than 8 tablets in 24 hours

children under 12 years: do not use

Other information

- store at 15º to 30ºC (59º to 86ºF)

Inactive ingredients

povidone, pregelatinized corn starch, sodium starch glycolate, stearic acid

Questions or comments?

call 516-341-0666,8:30 am - 4:30 pm ET, Monday - Friday

TAMPER EVIDENT: DO NOT USE IF IMPRINTED SAFETY SEAL UNDER CAP IS BROKEN OR MISSING

*Reliable 1 Laboratories LLC is not affiliated with the owner of the trademark TYLENOL®.

Relabeled and Repackaged by:

Enovachem PHARMACEUTICALS

Torrance, CA 90501